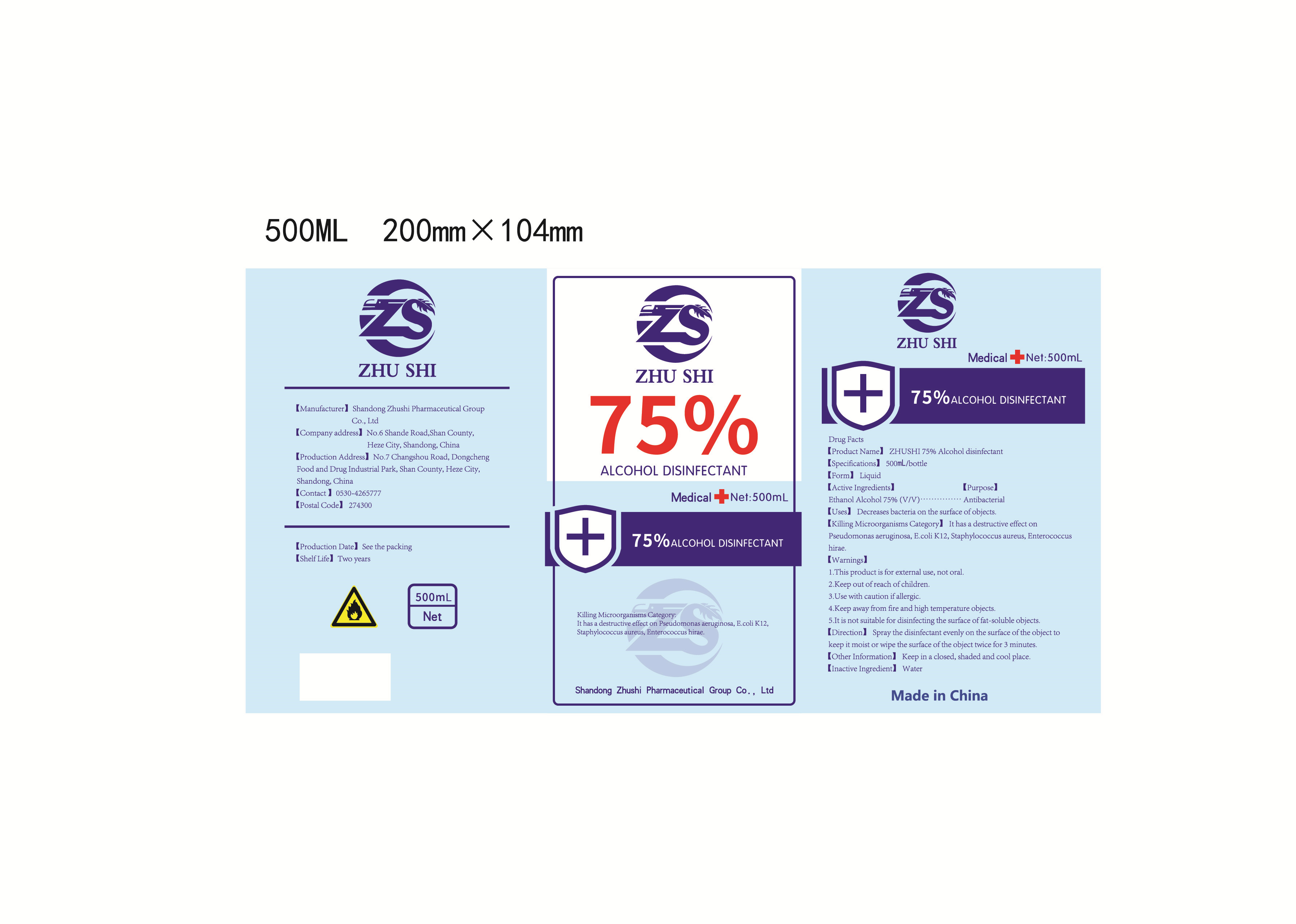 DRUG LABEL: ZHUSHI 75% Alcohol disinfectant
NDC: 56040-010 | Form: LIQUID
Manufacturer: Shandong Zhushi Pharmaceutical Group Co., Ltd.
Category: otc | Type: HUMAN OTC DRUG LABEL
Date: 20220310

ACTIVE INGREDIENTS: ALCOHOL 394.5 mL/500 mL
INACTIVE INGREDIENTS: WATER

Direction

Spray the disinfectant evenly on the surface of the object to keep it moist or wipe the surface of the object twice for 3 minutes.

INACTIVE INGREDIENT

water

Uses

Decreases bacteria on the surface of objects.

ACTIVE INGREDIENT

Ethanol Alcohol 75%

keep out of reach of children

PURPOSE

Antibacterial

WARNINGS

1.This product is for external use, not oral.
2.Keep out of reach of children.
3.Use with caution if allergic.
4.Keep away from fire and high temperature objects.
5.It is not suitable for disinfecting the surface of fat-soluble objects.

STORAGE AND HANDLING

Keep in a closed, shaded and cool place.